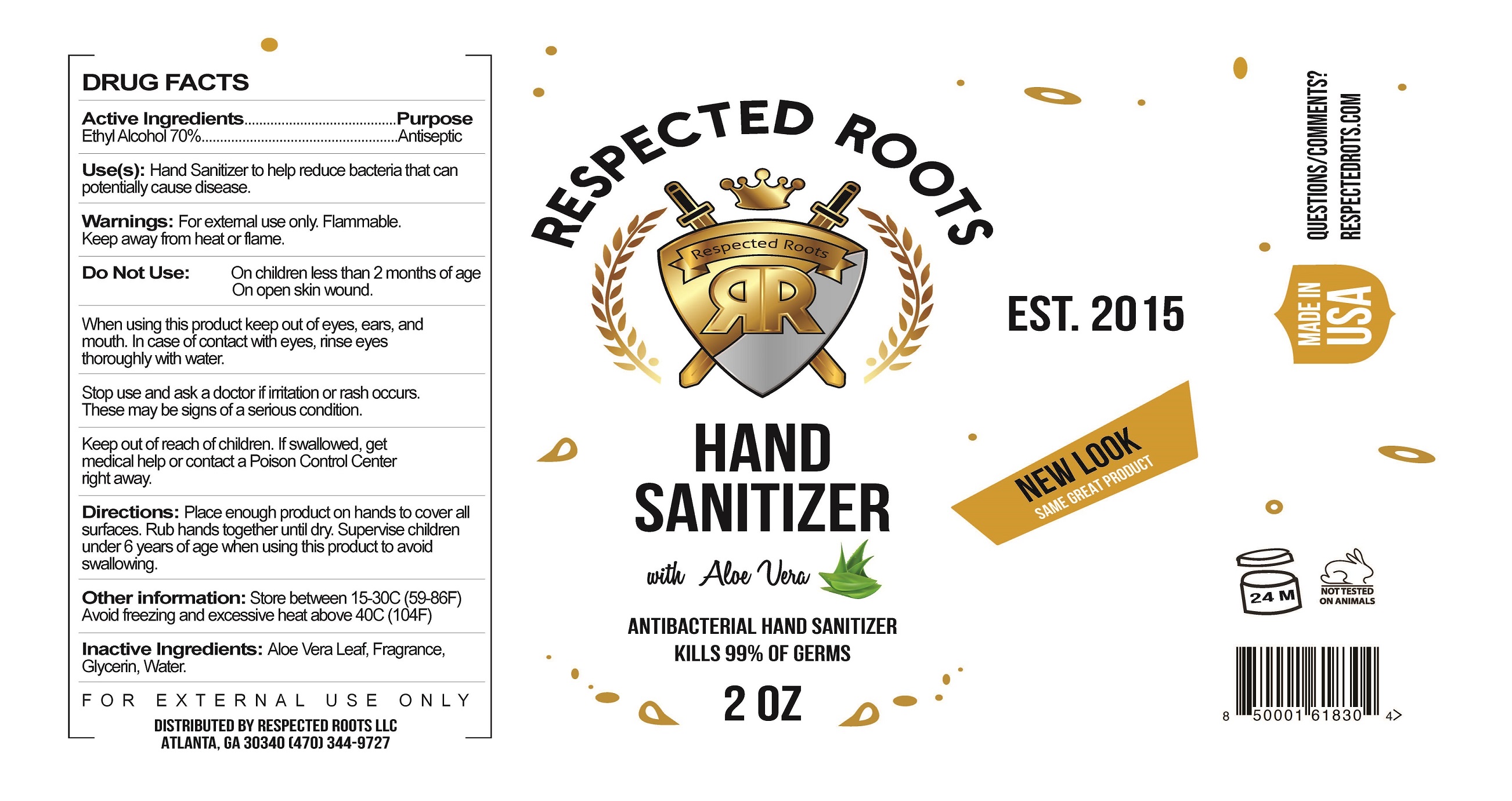 DRUG LABEL: Respected Roots Hand Sanitizer with Aloe Vera
NDC: 80028-0000 | Form: SOLUTION
Manufacturer: Respected Roots, LLC
Category: otc | Type: HUMAN OTC DRUG LABEL
Date: 20200820

ACTIVE INGREDIENTS: ALCOHOL 70 L/100 L
INACTIVE INGREDIENTS: GLYCERIN; ALOE VERA LEAF; WATER 18.425 L/100 L

Active Ingredient(s)

Alcohol 70% v/v. Purpose: Antiseptic

Purpose

Antiseptic

Use

Hand Sanitizer to help reduce bacteria that potentially can cause disease.

Warnings

For external use only. Flammable. Keep away from heat or flame

Do not use

- on children less than 2 months of age
- on open skin wounds

When using this product keep out of eyes, ears, and mouth. In case of contact with eyes, rinse eyes thoroughly with water.

Stop use and ask a doctor if irritation or rash occurs. These may be signs of a serious condition.

Keep out of reach of children. If swallowed, get medical help or contact a Poison Control Center right away.

Directions

Place enough product on hands to cover all surfaces. Rub hands together until dry.
Supervise children under 6 years of age when using this product to avoid swallowing.

Other information

- Store between 15-30C (59-86F)
- Avoid freezing and excessive heat above 40C (104F)

Inactive ingredients

Aloe Vera Leaf, Glycerin, Fragrance, Water